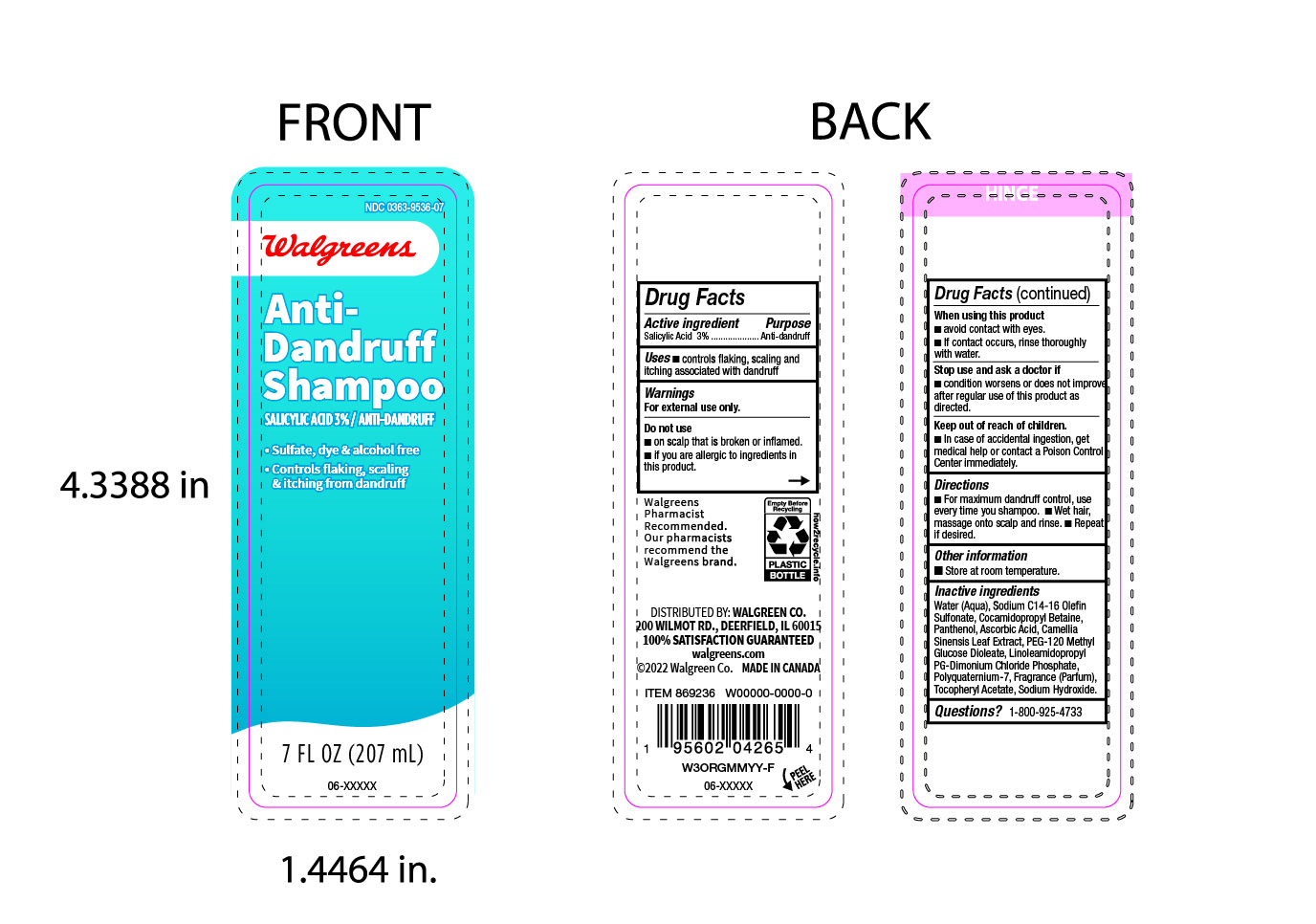 DRUG LABEL: Walgreens
NDC: 0363-9536 | Form: LOTION/SHAMPOO
Manufacturer: Walgreens
Category: otc | Type: HUMAN OTC DRUG LABEL
Date: 20250201

ACTIVE INGREDIENTS: SALICYLIC ACID 30 mg/1 mL
INACTIVE INGREDIENTS: ALPHA-TOCOPHEROL ACETATE; WATER; FRAGRANCE CLEAN ORC0600327; SODIUM HYDROXIDE; PANTHENOL; ASCORBIC ACID; PEG-120 METHYL GLUCOSE DIOLEATE; CAMELLIA SINENSIS LEAF; POLYQUATERNIUM-7; COCAMIDOPROPYL BETAINE; LINOLEAMIDOPROPYL PG-DIMONIUM CHLORIDE PHOSPHATE; SODIUM C14-16 OLEFIN SULFONATE

0363-9536-07 Walgreens Anti-Dandruff Shampoo

ACTIVE INGREDIENT

Salicylic Acid 3%

PURPOSE

Dandruff control

INDICATIONS AND USAGE

Controls flaking , scaling and itching from dandruff

WARNINGS

For external use only

DO NOT USE

- on scalp that is broken or inflammed
- if you are allergic to ingredients in this product

WHEN USING

- avoid contact with eyes.
- if contact occurs, rinse thoroughly with water.

Stop use and ask a doctor if

- condition worsens or does not improve after regular use of this product as directed.

KEEP OUT OF REACH OF CHILDREN

- in case of accidental ingestion, get medical help or contact a poison control centre immediately .

DOSAGE AND ADMINISTRATION

- For maximum dandruff control, use every time you shampoo.
- wet hair, massage onto scalp and rinse.
- Repeat if desired.

STORAGE AND HANDLING

Store at room temperature.

INACTIVE INGREDIENT

Water, Sodium C14-16 Olefin Sulfonate, Cocamidopropyl Betaine, Panthenol, Ascrobic Acid, Camellia Sinensis Leaf Extract, PEG-120 Methyl Glucose Dioleate, Linoleamidopropyl PG-Dimonium Chloride Phosphate, Polyquaternium-7, Fragrance (parfum), Tocopheryl Acetate, Sodium Hydroxide